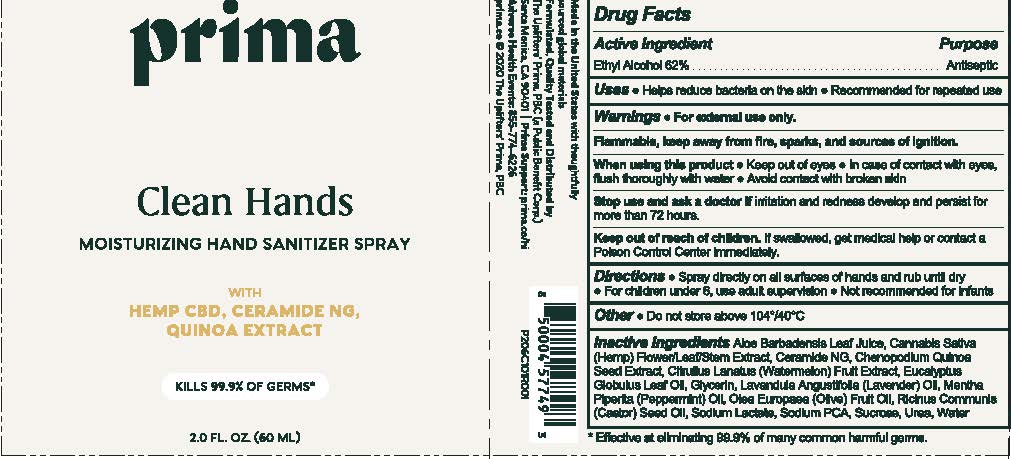 DRUG LABEL: Prima Clean Hands Moisturizing Hand SanitizerSpray
NDC: 76150-355 | Form: SPRAY
Manufacturer: Bell International Laboratories, Inc
Category: otc | Type: HUMAN OTC DRUG LABEL
Date: 20220413

ACTIVE INGREDIENTS: ALCOHOL 62 mL/100 mL
INACTIVE INGREDIENTS: CERAMIDE NG; WATERMELON; CHENOPODIUM QUINOA SEED; ALOE VERA LEAF; SUCROSE; SODIUM LACTATE; HEMP; EUCALYPTUS OIL; LAVENDER OIL; SODIUM PYRROLIDONE CARBOXYLATE; PEPPERMINT OIL; OLIVE OIL; CASTOR OIL; UREA; WATER; GLYCERIN

Prima Clean Hands Moisturizing Hand Sanitizer Spray

Active Ingredient

Ethyl Alcohol 62%

Purpose

Antiseptic

Uses

- Helps reduce bacteria on the skin
- Recommended for repeated use

Warnings

- For external use only
- Flammable, keep away from fire, sparks, and sources of ignition.
  - When using this product:
  - Keep out of eyes
  - In case of contact with eyes, flush thoroughly with water
  - Avoid contact with broken skin
  - Stop use and ask doctor if irritation and redness develop and persist for more than 72 hours.

KEEP OUT OF REACH OF CHILDREN

Keep out of reach with children. If swallowed, get medical help or contact a Poison Control Center immediately.

Directions

- Spray directly on all surfaces on hands and rub until dry
- For children under 6, use adult supervision
- Not recommended for infants

Inactive Ingredients

Aloe Barbadensis Leaf Juice

Cannabis Sativa (Hemp) Flower/Leaf/Stem Extract

Ceramide NG

Chenopodium Quinoa Seed Extract

Citrullus Lanatus (Watermelon) Fruit Extract

Eucalyptus Globulus Leaf Oil

Glycerin

Lavandula Angustifolia (Lavender) Oil

Mentha Piperita (Peppermint) Oil

Olea Europaea (Olive) Fruit Oil

Ricinus Communis (Castor) Seed Oil

Sodium Lactate

Sodium PCA

Sucrose

Urea

Water

Other

Do not store above 104°/ 40°C

PACKAGE LABEL

Made in the United States with thoughtfully sourced global materials

Formulated, Quality Tested and Distributed by The Uplifters' Prima, PBC (a Public Benefit Corp.)

Sanata Monica, CA 90401 | Prima Support: prima.co.hi

Adverse Health Events: 855-774-6226

prima.co © 2020 The Uplifters' Prima, PBC